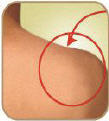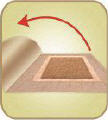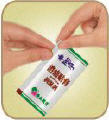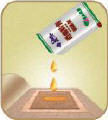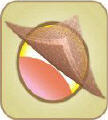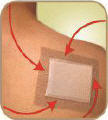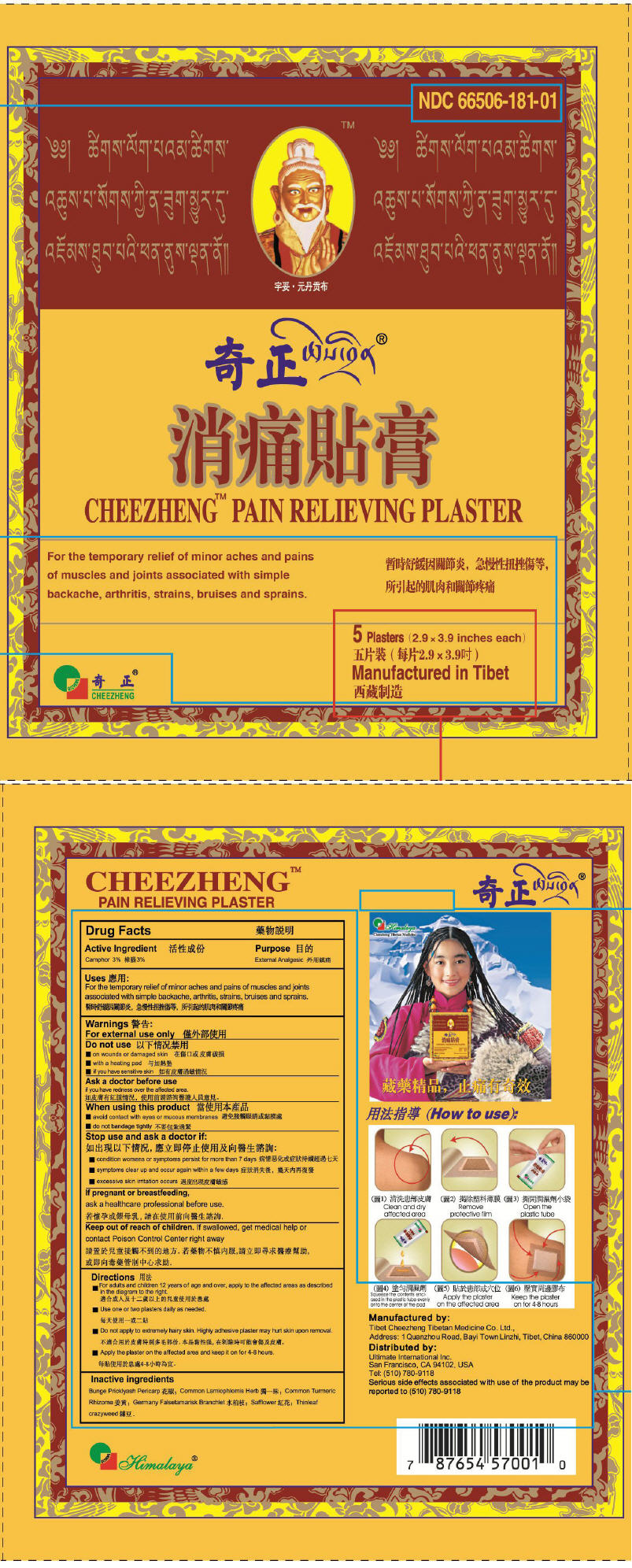 DRUG LABEL: Cheezheng Pain Relieving
NDC: 66506-181 | Form: PATCH
Manufacturer: Tibet Cheezheng Tibetan Medicine Co. Ltd.
Category: otc | Type: HUMAN OTC DRUG LABEL
Date: 20130123

ACTIVE INGREDIENTS: Camphor (Natural) 13.875 mg/1 h
INACTIVE INGREDIENTS: Zanthoxylum Bungeanum Fruit Rind; Safflower

CHEEZHENG™ PAIN RELIEVING PLASTER

Drug Facts

Active Ingredient

Camphor 3%

Purpose

External Analgesic

Uses

For the temporary relief of minor aches and pains of muscles and joints associated with simple backache, arthritis, strains, bruises and sprains.

Warnings

For external use only

Do not use

- on wounds or damaged skin
- with a heating pad
- if you have sensitive skin

Ask a doctor before use

if you have redness over the affected area.

When using this product

- avoid contact with eyes or mucous membranes
- do not bandage tightly

Stop use and ask a doctor if

- condition worsens or symptoms persist for more than 7 days
- symptoms clear up and occur again within a few days
- excessive skin irritation occurs

PREGNANCY OR BREAST FEEDING

If pregnant or breastfeeding, ask a healthcare professional before use.

Keep out of reach of children. If swallowed, get medical help or contact Poison Control Center right away

Directions

- For adults and children 12 years of age and over, apply to the affected areas as described in the diagram to the right.
- Use one or two plasters daily as needed.
- Do not apply to extremely hairy skin. Highly adhesive plaster may hurt skin upon removal.
- Apply the plaster on the affected area and keep it on for 4-8 hours.

(How to use)

(1) Clean and dry affected area

(2) Remove protective film

(3) Open the plastic tube

(4) Squeeze the contents enclosed in the plastic tube evenly onto the center of the pad

(5) Apply the plaster on the affected area

(6) Keep the plaster on for 4-8 hours

Inactive ingredients

Bunge Pricklyash Pericarp, Common Lamiophlomis Herb, Common Turmeric Rhizome, Germany Falsetamarisk Branchlet, Safflower, Thinleaf crazyweed.

Manufactured by:
Tibet Cheezheng Tibetan Medicine Co. Ltd.,
Address: 1 Quanzhou Road, Bayi Town Linzhi, Tibet, China 860000

Distributed by:
Ultimate International Inc.
San Francisco, CA 94102, USA

PRINCIPAL DISPLAY PANEL - 8 Hour Patch Label

NDC 66506-181-01

CHEEZHENG™ PAIN RELIEVING PLASTER

For the temporary relief of minor aches and pains
of muscles and joints associated with simple
backache, arthritis, strains, bruises and sprains.

5 Plasters (2.9 × 3.9 inches each)

Manufactured in Tibet

QIZHENG
CHEEZHENG